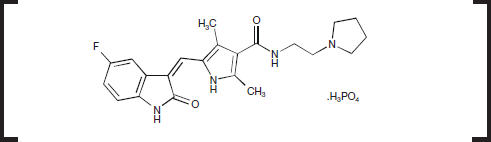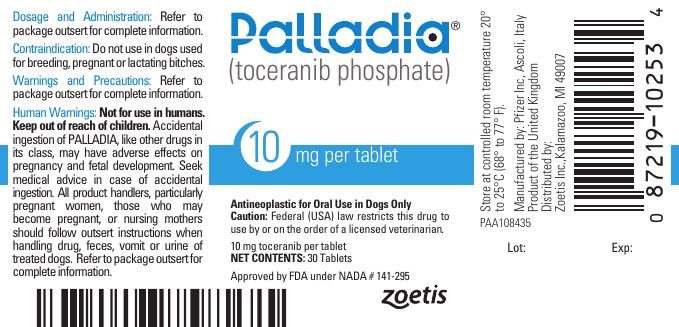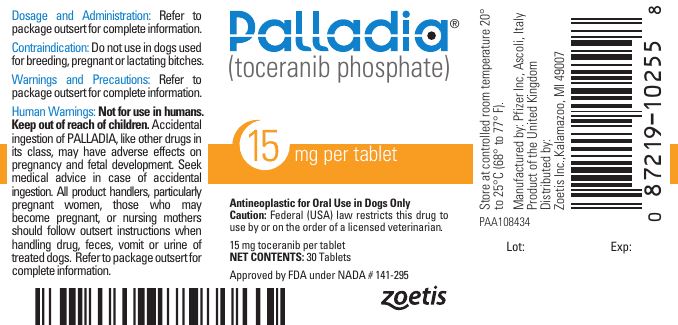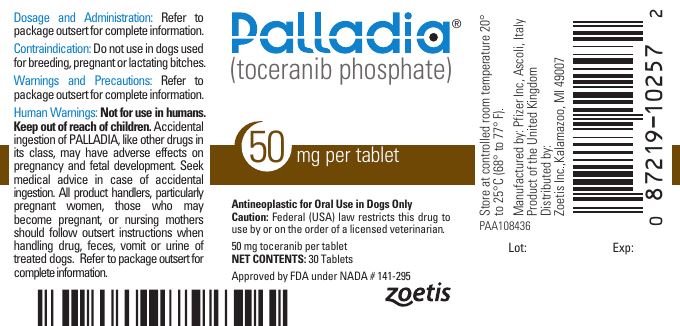 DRUG LABEL: Palladia
NDC: 54771-1690 | Form: TABLET
Manufacturer: Zoetis Inc.
Category: animal | Type: PRESCRIPTION ANIMAL DRUG LABEL
Date: 20220719

ACTIVE INGREDIENTS: TOCERANIB PHOSPHATE 10 mg/1 1

Palladia®
10 mg 15 mg 50 mg
(toceranib phosphate) Tablets

Antineoplastic
For oral use in dogs only

Caution

Federal (USA) law restricts this drug to use by or on the order of a licensed veterinarian.

Description

PALLADIA, a multi-kinase inhibitor targeting several receptor tyrosine kinases (RTK), is the phosphate salt of toceranib. The empirical formula is C22H25FN4O2H3O4P and the molecular weight is 494.46. The chemical name is (Z)-5-[(5-Fluoro-2-oxo-1,2-dihydro-3H -indol-3-ylidene)methyl]-2,4-dimethyl-N-(2-pyrrolidin-1-ylethyl)-1H-pyrrole-3-carboxamide phosphate. Toceranib phosphate is a small molecule with an indolinone chemical structure.

The chemical structure of toceranib phosphate is

Indications

PALLADIA tablets are indicated for the treatment of Patnaik grade II or III, recurrent, cutaneous mast cell tumors with or without regional lymph node involvement in dogs.

Dosage and Administration

Always provide Client Information Sheet with prescription. Administer an initial dosage of 3.25 mg/kg (1.48 mg/lb) body weight, orally every other day (see Table 1). Dose reductions of 0.5 mg/kg (to a minimum dose of 2.2 mg/kg (1.0 mg/lb) every other day) and dose interruptions (cessation of PALLADIA for up to two weeks) may be utilized, if needed, to manage adverse reactions (see Table 2 as well as Warnings and Precautions). Adjust dose based on approximately weekly veterinary assessments for the first 6 weeks and approximately every 6 weeks, thereafter. PALLADIA may be administered with or without food. Do not split tablets.

Table 1. 3.25 mg/kg Dose Chart
Dog Body Weight |  |  | Number of Tablets
Pounds | Kilograms | Dose | 10 mg | 15 mg | 50 mg
11.0 – 11.8 | 5.0 - 5.3 | 15 mg |  | 1
11.9 – 15.2 | 5.4 - 6.9 | 20 mg | 2
15.3 – 18.5 | 7.0 - 8.4 | 25 mg | 1 | 1
18.6 – 22.0 | 8.5 - 10.0 | 30 mg |  | 2
22.1 – 25.4 | 10.1 - 11.5 | 35 mg | 2 | 1
25.5 – 28.7 | 11.6 - 13.0 | 40 mg | 1 | 2
28.8 – 32.2 | 13.1 - 14.6 | 45 mg |  | 3
32.3 – 35.5 | 14.7 - 16.1 | 50 mg |  |  | 1
35.6 – 38.8 | 16.2 - 17.6 | 55 mg | 1 | 3
38.9 – 42.3 | 17.7 - 19.2 | 60 mg | 1 |  | 1
42.4 – 45.6 | 19.3 - 20.7 | 65 mg |  | 1 | 1
45.7 – 50.7 | 20.8 - 23.0 | 70 mg | 2 |  | 1
50.8 – 59.3 | 23.1 - 26.9 | 80 mg |  | 2 | 1
59.4 – 65.9 | 27.0 - 29.9 | 95 mg |  | 3 | 1
66.0 – 71.2 | 30.0 - 32.3 | 100 mg |  |  | 2
71.3 – 76.3 | 32.4 - 34.6 | 110 mg | 1 |  | 2
76.4 – 79.6 | 34.7 - 36.1 | 115 mg |  | 1 | 2
79.7 – 84.7 | 36.2 - 38.4 | 120 mg | 2 |  | 2
84.8 – 94.8 | 38.5 - 43.0 | 130 mg |  | 2 | 2
94.9 – 105.0 | 43.1 - 47.6 | 150 mg |  |  | 3
105.1 – 110.0 | 47.7 - 49.9 | 160 mg | 1 |  | 3
110.1 – 113.5 | 50.0 - 51.5 | 165 mg |  | 1 | 3
113.6 – 118.6 | 51.6 - 53.8 | 170 mg | 2 |  | 3
118.7 – 128.8 | 53.9 - 58.4 | 180 mg |  | 2 | 3
128.9 – 138.9 | 58.5 - 63.0 | 200 mg |  |  | 4
139.0 – 144.0 | 63.1 - 65.3 | 210 mg | 1 |  | 4
144.1 – 157.6 | 65.4 - 71.5 | 215 mg |  | 1 | 4
157.7 – 173.1 | 71.6 - 78.5 | 250 mg |  |  | 5
173.2 – 177.9 | 78.6 - 80.7 | 260 mg | 1 |  | 5
178.0 – 191.6 | 80.8 - 86.9 | 265 mg |  | 1 | 5
191.7 – 220.5 | 87.0 - 100.0 | 300 mg |  |  | 6

Table 2. Dose Modification Based on Toxicity Observed
Toxicity | Dose Adjustment
Neutropenia
>1000/µL | Maintain dose level
≤1000/µL or neutropenic fever or infection | Stop drug until >1000/µL and clinical signs normal; then decrease dose by 0.5 mg/kg
Renal Toxicities (Creatinine)
<2.0 mg/dL | Maintain dose level
≥2.0 mg/dL | Stop drug until <2.0 mg/dL then decrease dose by 0.5 mg/kg
Albumin
<1.5 g/dL | Stop drug until >2.5 g/dL then decrease dose by 0.5 mg/kg
Hematocrit
<26% | Stop drug until >30% then decrease dose by 0.5 mg/kg
Diarrhea
<4 watery stools/day for less than 2 days | Maintain dose level and institute supportive care
≥4 watery stools/day or ≥ 2 days | Stop drug until formed stools and institute supportive care. When dosing is resumed, decrease dose by 0.5 mg/kg
GI Bleeding
Fresh blood in stool or black tarry stool for > 2 days or frank hemorrhage or blood clots in stool. | Stop drug and institute supportive care until resolution of all clinical signs of blood in stool, then decrease dose by 0.5 mg/kg.

Contraindications

Do not use in dogs used for breeding, or for pregnant or lactating bitches (see Clinical Pharmacology).

Warnings

PALLADIA may cause vascular dysfunction which can lead to edema and thromboembolism, including pulmonary thromboembolism. Discontinue drug until clinical signs and clinical pathology have normalized. To assure vasculature homeostasis, wait at least 3 days after stopping drug before performing surgery (see Adverse Reactions).

Serious and sometimes fatal gastrointestinal complications including gastrointestinal perforation have occurred rarely in dogs treated with PALLADIA (see Adverse Reactions). If gastrointestinal ulceration is suspected, stop drug administration and treat appropriately.

Human Warnings

NOT FOR USE IN HUMANS. KEEP THIS AND ALL MEDICATIONS OUT OF THE REACH OF CHILDREN. Children should not come in contact with PALLADIA. Keep children away from feces, urine, or vomit of treated dogs. To avoid exposure to drug, wash hands with soap and water after administering PALLADIA and wear protective gloves to prevent direct contact with feces, urine, vomit, and broken or moistened PALLADIA tablets. Place all waste materials in a plastic bag and seal before general disposal. If eyes are accidentally exposed to the drug, rinse eyes with water immediately. In case of accidental ingestion by a person, seek medical advice immediately, show the package insert or label to the physician. Gastrointestinal discomfort such as vomiting or diarrhea may occur if this drug is accidentally ingested.

Pregnant women, women who may become pregnant, or nursing mothers should pay special attention to these handling precautions. (See handling instructions above.) PALLADIA, like other drugs in its class, prevents the formation of new blood vessels in tumors. In a similar manner, PALLADIA may affect blood vessel formation in the developing fetus and may harm an unborn baby (cause birth defects). For pregnant women, accidental ingestion of PALLADIA may have adverse effects on pregnancy.

Precautions

Temporarily discontinue the use of PALLADIA if anemia, azotemia, hypoalbuminemia, and hyperphosphatemia occur simultaneously. Resume treatment at a dose reduction of 0.5 mg/kg after 1 to 2 weeks when values have improved and albumin is >2.5 g/dL. Temporary treatment interruptions may be needed if any one of these occurs alone: hematocrit <26%, creatinine ≥2.0 mg/dL or albumin <1.5 g/dL. Then resume treatment at a dose reduction of 0.5 mg/kg once the hematocrit is >30%, the creatinine is <2.0 mg/dL, and the albumin is >2.5 g/dL.

Temporarily discontinue the use of PALLADIA if neutrophil count is ≤1000/μL. Resume treatment after 1 to 2 weeks at a dose reduction of 0.5 mg/kg, when neutrophil count has returned to >1000/μL. Further dose reductions may be needed if severe neutropenia reoccurs.

The presence of systemic mast cell tumor prior to treatment may predispose a dog to clinically significant mast cell degranulation with possible severe systemic adverse reactions when treated with PALLADIA. Attempts should be made to rule out systemic mastocytosis prior to initiation of treatment with PALLADIA.

PALLADIA has been associated with severe diarrhea or GI bleeding that requires prompt treatment. Dose interruptions and dose reductions may be needed depending upon the severity of clinical signs. (See Table 2 in Dosage and Administration.)

Use non-steroidal anti-inflammatory drugs with caution in conjunction with PALLADIA due to an increased risk of gastrointestinal ulceration or perforation.

PALLADIA is metabolized in the liver. Co-administration of PALLADIA with strong inhibitors of the CYP3A4 family may increase PALLADIA concentrations. The effect of concomitant medications that may inhibit the metabolism of PALLADIA has not been evaluated. Drug compatibility should be monitored in patients requiring concomitant medications.

The safe use of PALLADIA has not been evaluated in dogs less than 24 months of age or weighing less than 5 kg.

Adverse Reactions

A US clinical field study comprised of a 6-week masked phase, followed by an open-label phase, evaluated the safety and effectiveness of PALLADIA in 151 client-owned dogs that had Patnaik grade II or III, recurrent, cutaneous mast cell tumors with or without regional lymph node involvement. The most common adverse reactions reported during the masked phase are summarized in Table 3; those reported during the entire study (masked phase combined with the open-label phase) are summarized in Table 4.

Table 3. Summary of the most common adverse reactions during the masked phase [The mean time on study during the masked phase was 37.0 days for PALLADIA-treated dogs (median, 42.0 days) and 27.6 days for placebo-treated dogs (median, 21.0 days); no adjustments were made in the statistical comparisons for this disparity.]
 | Placebo (n = 64) |  | PALLADIA (n = 87)
Adverse Reaction | Any Grade [Investigators assigned severity grade of 1, 2, 3 or 4 (1 - least severe; 4 - most severe).] | Grade 3 or 4 | Any Grade | Grade 3 or 4
Diarrhea | 26.6% | 3.1% | 46.0% | 6.9%
Anorexia | 31.3% | 6.3% | 39.1% | 6.9%
Lethargy | 29.7% | 3.1% | 35.6% | 4.6%
Vomiting | 32.8% | 6.3% | 32.2% | 9.2%
Lameness | 9.4% | 0.0% | 17.2% | 0.0%
Weight loss | 3.1% | 0.0% | 14.9% | 1.1%
Blood in stool/GI bleed/hemorrhagic diarrhea | 3.1% | 0.0% | 12.6% | 2.3%
Musculoskeletal disorder | 6.3% | 0.0% | 11.5% | 1.1%
Dehydration | 4.7% | 0.0% | 9.2% | 2.3%
Dermatitis | 9.4% | 1.6% | 9.2% | 0.0%
Pruritus | 4.7% | 0.0% | 9.2% | 0.0%
Tachypnea | 4.7% | 0.0% | 8.0% | 1.1%
Localized pain | 4.7% | 0.0% | 8.0% | 0.0%
Nausea | 3.1% | 0.0% | 8.0% | 1.1%
General pain | 4.7% | 1.6% | 6.9% | 0.0%
Polydipsia | 7.8% | 0.0% | 6.9% | 0.0%
Pyrexia | 3.1% | 0.0% | 5.7% | 2.3%
Flatulence | 3.1% | 0.0% | 5.7% | 0.0%
Pigmentation disorder | 1.6% | 0.0% | 5.7% | 0.0%
Laboratory Abnormality | Any Grade [Grading of laboratory abnormalities was based on the National Cancer Institute's Common Toxicity Criteria guideline adapted for canines (1 - least severe; 4 - most severe).] | Grade 3 or 4 | Any Grade | Grade 3 or 4
Neutropenia | 6.3% | 0.0% | 46.0% | 0.0%
Thrombocytopenia | 20.3% | 0.0% | 24.1% | 0.0%
Increased alanine aminotransferase | 21.9% | 4.7% | 24.1% | 1.1%
Hypoalbuminemia | 7.8% | 0.0% | 12.6% | 0.0%
Decreased hematocrit | 7.8% | 0.0% | 5.7% | 3.4%
Hyperbilirubinemia | 1.6% | 1.6% | 5.7% | 0.0%
Increased creatinine | 4.7% | 0.0% | 5.7% | 0.0%
Urinary tract infection | 1.6% | 0.0% | 5.7% | 0.0%

Table 4. Summary of the most common adverse reactions during the study (masked phase combined with the open-label phase) [The duration of treatment with PALLADIA ranged from 2 to 812 days (mean, 144 days; median, 68 days). All dogs received at least 1 dose of PALLADIA.]
 | PALLADIA (n = 145)
Adverse Reactions | Any Grade [Investigators assigned severity grade of 1, 2, 3 or 4 (1 – least severe; 4 – most severe).] | Grade 3 or 4
Diarrhea | 58.6% | 8.3%
Anorexia | 49.7% | 8.3%
Vomiting | 47.6% | 9.7%
Lethargy | 39.3% | 4.1%
Lameness | 22.8% | 0.0%
Weight loss | 21.4% | 2.8%
Blood in stool/GI bleed/hemorrhagic diarrhea | 18.6% | 2.8%
Dehydration | 15.2% | 2.1%
Pruritus | 12.4% | 0.0%
Pigmentation disorder | 11.7% | 0.0%
Dermatitis | 11.0% | 0.0%
Musculoskeletal disorder | 11.0% | 0.0%
General pain | 8.3% | 0.0%
Otitis externa | 8.3% | 0.0%
Tachypnea | 8.3% | 0.0%
Nausea | 7.6% | 1.4%
Polydipsia | 7.6% | 0.0%
Pyrexia | 6.9% | 2.8%
Arthritis | 6.2% | 0.0%
Localized edema | 6.2% | 0.0%
Bacterial skin infection | 5.5% | 0.0%
Conjunctivitis | 5.5% | 0.0%
Laboratory Abnormality | Any Grade [Grading of laboratory abnormalities was based on the National Cancer Institute's Common Toxicity Criteria guideline adapted for canines (1 – least severe; 4 – most severe).] | Grade 3 or 4
Neutropenia | 44.8% | 1.4%
Hypoalbuminemia | 28.3% | 1.4%
Thrombocytopenia | 28.3% | 2.1%
Increased alanine aminotransferase | 27.6% | 4.1%
Decreased hematocrit | 11.0% | 2.8%
Increased creatinine | 13.8% | 1.4%
Hyperbilirubinemia | 6.9% | 0.0%
Urinary tract infection | 7.6% | 0.0%
Other adverse events were reported but occurred in < 5% of dogs. Any individual dog may have had multiple adverse events.

There were 5 deaths during this study that were possibly drug related. Pathology findings generally revealed evidence of vascular dysfunction including pulmonary thromboembolism (post-operative); multi-organ failure associated with vasculitis and thrombosis; vascular thrombosis with disseminated intravascular coagulopathy (DIC) and pancreatitis; and vasculitis with DIC. One dog died secondary to gastric perforation; the duration of treatment with PALLADIA was 221 days and there was no evidence of mast cell tumor at necropsy. These deaths occurred in the presence or absence of gross-disease; treatment durations ranged from 18 to 221 days.

The relationship of the following deaths to drug are unknown. One dog, first treated for 3 weeks with a placebo, died of unknown cause 7 days after initiation of PALLADIA therapy. Another dog died of unknown cause 92 days after initiation of PALLADIA therapy. No necropsy was conducted in either dog.

Twenty seven dogs developed some form of gastrointestinal bleeding with 2.8% of dogs having severe bleeding. One dog developed gastric ulceration which was possibly drug related. Three dogs died from gastric (1 dog) or duodenal (2 dogs) perforations during the study. One dog with a duodenal perforation received only 1 dose of study drug and, therefore, was not considered drug related.

Seven dogs developed nasal depigmentation within the first few weeks of treatment. Eleven dogs developed coat color or skin changes during the study. Two of these dogs had complete coat color changes from fawn to white and from deep red to blonde. Seven dogs experienced alopecia.

There is a drug related effect on body weight: 20.0% of dogs had >13% weight loss in the masked plus open-label phase attributable to drug. Of these, 5 dogs had >25% weight loss. Three dogs had seizure-like activity while on study drug. It can not be determined if these were drug related.

Two dogs developed epistaxis that was not associated with thrombocytopenia. Another dog developed epistaxis with concurrent disseminated intravascular coagulopathy.

For a copy of the Material Safety Data Sheet (MSDS) or to report adverse events call Zoetis at 1-888-963-8471.

Information for Dog Owners

Always provide Client Information Sheet with prescription and review with owners. Owners should be advised on possible adverse reactions and when to stop drug and call the veterinarian. Owners should be advised of the handling instructions.

Clinical Pharmacology

Mechanism of Action

Toceranib phosphate is a small molecule that has both direct antitumor and antiangiogenic activity. In non-clinical pharmacology studies, toceranib selectively inhibited the tyrosine kinase activity of several members of the split kinase receptor tyrosine kinase (RTK) family, some of which are implicated in tumor growth, pathologic angiogenesis, and metastatic progression of cancer. Toceranib inhibited the activity of Flk-1/KDR tyrosine kinase (vascular endothelial growth factor receptor, VEGFR2), platelet-derived growth factor receptor (PDGFR), and stem cell factor receptor (Kit) in both biochemical and cellular assays. Toceranib has been shown to exert an antiproliferative effect on endothelial cells in vitro. Toceranib treatment can induce cell cycle arrest and subsequent apoptosis in tumor cell lines expressing activating mutations in the split kinase RTK, ckit. Canine mast cell tumor growth is frequently driven by activating mutations in c-kit.^(1, 2)

Other compounds in the antiangiogenesis class of antineoplastic agents are known to increase embryolethality and fetal abnormalities. As angiogenesis is a critical component of embryonic and fetal development, inhibition of angiogenesis following administration of PALLADIA should be expected to result in adverse effects on the pregnancy in the bitch.

Pharmacokinetics

Following intravenous administration, the pharmacokinetics of toceranib is characterized by a very large volume of distribution (>20 L/kg, indicating partitioning into tissues), a terminal elimination half-life of about 16 hrs, and a clearance of >1 L/hr/kg. With a regimen of 3.25 mg free base equivalent (fbe)/kg doses of toceranib administered by tablet orally every other day for 2 weeks (7 doses), the pharmacokinetic parameters of toceranib in plasma in healthy Beagle dogs (between 7.2 – 12.5 kg) are shown in the table below.

Table 5. Pharmacokinetic Parameters
Pharmacokinetic Parameters (Mean + 1SD) | Total (n=11;6M, 5F) Dose 1 | Total (n=10; 5M, 5F) Dose 7
Elimination half-life, t1/2 (h) | 16.4 ± 3.6 | 17.2 ± 3.9
Time to maximum plasma concentration, Tmax (h) | 5.3 ± 1.6 | 6.2 ± 2.6
Maximum plasma concentration, Cmax (ng/mL) | 86 ± 22 | 109 ± 41
Cmin (ng/mL) [Dose-normalized value (adjusted to 3.25 mg/kg dose)] , [Cmin is the concentration at 48 h post-dose, which corresponds to the dose interval.] | 12.7 ± 6.0 | 18.7 ± 8.3
Area under the plasma concentration time-curve, AUC0-48 (ng∙h/mL) | 1833 ± 508 | 2635 ± 939

Oral bioavailability of toceranib is 77%. PALLADIA is highly protein bound at 91% to 93%.

It should be noted that despite the homogeneity of subjects included in this study, large between-subject variability was observed. Regardless of the route of administration, linear pharmacokinetics has been observed at doses up to 5 mg/kg twice daily. Using an in vitro hepatocyte and liver microsome test system, the Z isomer was found to be metabolized to the N-oxide derivative of toceranib in dogs, humans, cats, and rats. Although a small gender difference was observed in the in vitro study (81% conversion in male dogs, 56% conversion in female dogs) no differences in toceranib pharmacokinetics was observed in vivo. The effects of renal impairment, hepatic impairment or breed on the pharmacokinetics of toceranib have not been investigated.

Effectiveness

The effectiveness and safety of PALLADIA oral tablets for the treatment of mast cell tumors was evaluated in a randomized, placebo-controlled, double-masked, multicenter clinical field study. The purpose of this study was to evaluate the effectiveness and safety of PALLADIA in the treatment of mast cell tumors in dogs that had recurrent measurable disease after surgery and to evaluate objective response (complete or partial response). PALLADIA treatment was compared to placebo treatment using response rates at the end of the 6-week masked phase. Response rates were determined using the National Cancer Institute's Response Evaluation Criteria in Solid Tumors Guideline^3 which was modified specifically for the evaluation of canine mast cell tumors.

One-hundred-fifty-three dogs were randomly assigned to treatment with either 3.25 mg/kg PALLADIA (n = 88) or placebo (n = 65) orally, every other day for 6 weeks, or until disease progression or withdrawal from the study for another cause. Treatment was unmasked at the time of disease progression: dogs receiving placebo were then offered crossover to open-label PALLADIA; dogs receiving PALLADIA were discontinued from the study. Dogs were required to have Patnaik grade II or III, recurrent, cutaneous mast cell tumors with or without regional lymph node involvement. At least 1 tumor had to be at least 20 mm in diameter. Dogs had a limit of 1 completed radiation protocol and a limit of 1 prior systemic chemotherapy regimen. Dogs with evidence of systemic mast cell tumor were excluded. Treatment with systemic corticosteroids during the study or within 14 days prior to study initiation was not permitted. If needed to manage adverse reactions, dose interruptions (cessation of PALLADIA for up to 2 weeks) were prescribed and/or dosage was reduced to as low as 2.2 mg/kg.

The effectiveness analysis showed a statistically significant advantage for PALLADIA over placebo in the primary effectiveness endpoint of objective response at the end of the six week masked phase. Objective response is complete response + partial response. Partial response is ≥ 30% decrease in the sum of the longest diameter of target lesions, taking as reference the baseline sum, non-progression of nontarget lesions and appearance of no new lesions.

Mast Cell Tumor – Primary Effectiveness Endpoint Results
Effectiveness Parameter | Placebo (n = 63) | PALLADIA (n = 86) | P-value
Objective Response Rate [The difference in objective response rate between groups was not significantly associated with tumor burden (presence vs. absence of regional lymph node involvement) or tumor grade (P > 0.05).] | 7.9% | 37.2% | < 0.001

During the study, PALLADIA was administered concomitantly with other medications such as antimicrobials, H-2 receptor blockers, antihistamines, anti-emetics, non-steroidal antiinflammatory drugs, locally-acting anti-ulcer medications, opiate gastrointestinal motility modifiers, opioids, vaccines, anthelmintics, antiparasitics, and topical/ophthalmic/otic corticosteroid preparations. During the open-label phase only, 5 dogs received a brief course of short-acting corticosteroids.

Animal Safety

In the target animal safety study presented below, PALLADIA was demonstrated to have a narrow margin of safety; dogs being treated with PALLADIA should be monitored for adverse reactions which may indicate a dose adjustment is required. Two dogs in the 6 mg/kg group were euthanized for clinical toxicities on Days 23 and 27 of the study, respectively.

Toceranib was administered orally to 20 male and 20 female adult Beagle dogs (approximately 2 years of age) at doses of 0 mg/kg (placebo, 12 dogs), 2 mg/kg (0.5×, 8 dogs), 4 mg/kg (1×, 12 dogs), or 6 mg/kg (1.5×, 8 dogs) once every other day for 13 consecutive weeks without dose interruption. Toceranib caused weight loss, decreased feed consumption, pancreatic, gonadal, adrenal, muscle, and hematopoietic changes.

Feed consumption was decreased in the 6 mg/kg group compared to placebo, with the largest difference in means occurring at Day 35. Decrease in body weights in the 4 mg/kg group were seen at Day 31 and in the 6 mg/kg group at Day 15 compared with placebo and continued through the study. Dose related lameness, observed almost exclusively in the hind limbs, and limb pain was greater in all treatment groups as compared to placebo, with the 6 mg/kg group demonstrating the highest incidence. Stiffness and weakness were noted to occur almost exclusively in the 6 mg/kg group. Redness of oral mucosa was observed in all treatment groups. One dog in the 4 mg/kg group had oral ulcerations and one dog in the 6 mg/kg group had skin ulcerations, both with bacterial infections present. Diarrhea or soft stool were seen in all four groups.

Hematology analyses showed decreases in hematocrit, hemoglobin, and erythrocyte count and a decrease in reticulocyte count in the 4 and 6 mg/kg groups that tended to recover sufficiently to limit further erythrocyte count decreases. White blood cell counts were significantly lower across the study in all treated groups compared to placebo, primarily due to a decrease in neutrophils. Lymphocytes decreased to a lesser degree, especially at the low dose. Eosinophils and basophils showed marked, persistent decreases. Monocytes were not affected.

Platelet counts increased slightly in 4 and 6 mg/kg groups. Increases were observed in fibrinogen in the 4 and 6 mg/kg group.

Increases were observed in aspartate aminotransferase, creatine kinase, and serum phosphorus concentrations in the 4 and 6 mg/kg groups. Increases in alkaline phosphatase were seen in the 6 mg/kg group. An increase in amylase was seen in one dog in each of the treatment groups. An increase in serum potassium was seen in one dog in the 6 mg/kg group. Increases in lactate dehydrogenase and globulins were observed in the 6 mg/kg group.

Treatment-related microscopic changes included slight to marked reduction in cellularity of sternal and femoral bone marrow. There was a corresponding mild extramedullary hematopoiesis, mainly erythropoiesis, in the spleen. In the pancreas, dose-related slight to moderate acinar degranulation, characterized by diffuse loss of zymogen granules, occurred. In the adrenal glands, minimal cortical congestion/hemorrhage occurred at all doses, with suggestive dose-relationship. Adrenal cortical vacuolation was noted with low frequency in all groups. Dose related changes were noted in reproductive organs of both sexes. Males showed a dose-related germ cell depletion, tubular vacuolation, and reductions in numbers of mature spermatozoa. In females, ovaries showed a reduced incidence of mature/regressing corpora lutea and an increased incidence of small follicles.

Two dogs (one male, one female) in the 6 mg/kg group were euthanized for treatment-related clinical toxicities on Days 23 and 27 of the study, respectively. Onset of the terminal syndrome was seen as markedly reduced feed intake and melena. Over the following 9 days, the decreased feed intake progressed to near-complete anorexia and hematochezia appeared. Weight loss, lethargy, hindlimb lameness and weakness were observed. The following clinical pathology results are consistent with changes seen in the other dogs in the 6 mg/kg group as well as changes due to the dogs' debilitated conditions just prior to euthanasia. Both dogs had increases in total protein, globulins, phosphorus, cholesterol, triglycerides and fibrinogen. One dog had pancytopenia, decreased hematocrit, hemoglobin, reticulocytes, albumin, and PT and increased bands. Hematuria was also present. The other dog also had decreased lymphocytes, eosinophils, chloride, and sodium and increases in RBC, hematocrit, hemoglobin, platelets, ALP, amylase, creatinine, BUN, magnesium, potassium, and total bilirubin. Clotting profile showed a decreased PT and increased in PTT in both dogs. These dogs showed lymphoid depletion in lymph nodes, thymus, and gut-associated lymphatic tissues and mild to marked gastrointestinal lesions in addition to the microscopic findings described in animals surviving to the end of the study. These two dogs also had lesions in the gastrointestinal tract, kidneys, pancreas, pituitary gland and adrenal glands.

Storage Conditions

Store at controlled room temperature 20° to 25° C (68° to 77° F).

How Supplied

PALLADIA tablets contain 10 mg, 15 mg, or 50 mg of toceranib as toceranib phosphate per tablet. The tablets are packaged in 30 count bottles.

References

- London CA, Hannah AL, Zadovoskaya R, et al. Phase I Dose-Escalating Study of SU11654, a Small Molecule Receptor Tyrosine Kinase Inhibitor, in Dogs with Spontaneous Malignancies. Clinical Cancer Research 9(7):2755-2768; 2003
- Pryer NK, Lee LB, Zadovoskaya R, et al. Proof of Target for SU11654: Inhibition of KIT phosphorylation in Canine Mast Cell Tumors. Clinical Cancer Research 9(15):5729- 5734; 2003
- http://ctep.cancer.gov/protocolDevelopment/

Approved by FDA under NADA # 141-295

Manufactured by: Pfizer Inc, Ascoli, Italy

Product of the United Kingdom
Distributed by:
Zoetis Inc.,Kalamazoo, MI 49007

Revised: November 2018

PAA108433

Client Information Sheet

Palladia®
(toceranib phosphate) Tablets

This summary contains important information about PALLADIA. You should read this information before you start giving your dog PALLADIA and review it each time the prescription is refilled as there may be new information. This sheet is provided only as a summary and does not take the place of instructions from your veterinarian. Talk with your veterinarian if you do not understand any of this information or if you want to know more about PALLADIA.

What is PALLADIA?

- PALLADIA, a tyrosine kinase inhibitor, is a drug used to treat mast cell tumors, a common form of cancer that affects dogs.
- PALLADIA works in two ways:
  - By killing tumor cells.
  - By cutting off the blood supply to the tumor.
- Your veterinarian has decided to include PALLADIA as a part of your dog's treatment plan for mast cell tumor. Other types of treatment, such as surgery, drug treatment and/or radiation may be included in the plan. Be sure to speak with your veterinarian about all parts of your dog's treatment plan.

What do I need to tell my veterinarian about my dog before administering PALLADIA?

- Tell your veterinarian about all other medications your pet is taking, including: prescription drugs; over the counter drugs; heartworm, flea & tick medications; vitamins and supplements, including herbal medications.
- Tell your veterinarian if your dog is pregnant, nursing puppies, or is intended for breeding purposes.

How do I give PALLADIA to my dog?

- PALLADIA should be given to your dog by mouth (orally).
- PALLADIA may be hidden inside a treat; be certain your dog swallows the entire tablet(s).
- Follow your veterinarian's instructions for how much and how often to give PALLADIA.
- See the Handling Instructions section below in order to administer PALLADIA safely to your dog.

How will PALLADIA affect my dog?

- PALLADIA may help shrink your dog's tumor. Like other cancer treatments, it can be difficult to predict whether your dog's tumor will respond to PALLADIA, and if it does respond, how long it will remain responsive to PALLADIA. Regular check ups by your veterinarian are necessary to determine whether your dog is responding as expected, and to decide whether your dog should continue to receive PALLADIA.

What are some possible side effects of PALLADIA?

- Like all drugs, PALLADIA may cause side effects, even at the prescribed dose. Serious side effects can occur, with or without warning, and may in some situations result in death.
  - The most common side effects which may occur with PALLADIA include diarrhea, decreased/loss of appetite, lameness, weight loss and blood in the stool.
- Stop PALLADIA immediately and contact your veterinarian if you notice any of the following changes in your dog:
  - Refusal to eat
  - Vomiting or watery stools (diarrhea), especially if more frequent than twice in 24 hours
  - Black tarry stools
  - Bright red blood in vomit or stools
  - Unexplained bruising or bleeding
  - Or if your dog experiences other changes that concern you
- There are other side effects which may occur. For a more complete list, ask your veterinarian.

Handling Instructions

What do I need to know to handle PALLADIA safely?

Because PALLADIA is an anti-cancer drug, extra care must be taken when handling the tablets, giving the drug to your dog, and cleaning up after your dog.

- PALLADIA is not for use in humans.
- You should keep PALLADIA in a secure storage area out of the reach of children.
- Children should not come in contact with PALLADIA. Keep children away from feces, urine, or vomit of treated dogs.
- If you are pregnant, a nursing mother, or may become pregnant and you choose to administer PALLADIA to your dog, you should be particularly careful and follow the handling procedures described below.
- PALLADIA prevents the formation of new blood vessels in tumors. In a similar manner, PALLADIA may affect blood vessel formation in the developing fetus and may harm an unborn baby (cause birth defects). For pregnant women, accidental ingestion of PALLADIA may have adverse effects on pregnancy.
- If PALLADIA is accidentally ingested by you or a family member, seek medical advice immediately. It is important to show the treating physician a copy of the package insert or label. In cases of accidental human ingestion of PALLADIA, you may experience gastrointestinal discomfort, including vomiting or diarrhea.

The following handling procedures will help to minimize exposure to the active ingredient in PALLADIA for you and other members of your household:

- Anyone who administers PALLADIA to your dog should wash their hands after handling tablets.
- When you or others are handling the tablets:
  - Do not split or break the tablets to avoid disrupting the protective film coating.
  - PALLADIA tablets should be administered to your dog immediately after they are removed from the bottle.
  - Protective gloves should be worn if handling broken or moistened tablets. If your dog spits out the PALLADIA tablet, the tablet will be moistened and should be handled with protective gloves.
  - If the PALLADIA tablet is "hidden" in food, make sure that your dog has eaten the entire dose. This will minimize the potential for exposure to children or other household members to PALLADIA.
- Cleaning up after your dog:
  - Because PALLADIA is present in the stool, urine and vomit of dogs under treatment, you must wear protective gloves to clean up after your treated dog.
  - While your dog receives PALLADIA, place the stool, feces or vomit, and any disposable towels used to clean up in a plastic bag which should be sealed for general household disposal. This will minimize the potential for exposure to people in contact with the trash.
  - You should not wash any items soiled with stool, urine or vomit from your dog with other laundry.

This client information sheet gives the most important information about PALLADIA. For more information about PALLADIA, talk with your veterinarian.

To report a suspected adverse reaction call Zoetis at 1-888-963-8471.

Manufactured by: Pfizer Inc, Ascoli, Italy

Product of the United Kingdom
Distributed by:
Zoetis Inc.,Kalamazoo, MI 49007

Revised: November 2018

PAA108433

PRINCIPAL DISPLAY PANEL - 10 mg Tablet Bottle Label

Palladia®
(toceranib phosphate)

10 mg per tablet

Antineoplastic for Oral Use in Dogs Only
Caution: Federal (USA) law restricts this drug to
use by or on the order of a licensed veterinarian.

10 mg toceranib per tablet
NET CONTENTS: 30 Tablets

Approved by FDA under NADA # 141-295

zoetis

Palladia 10mg

PRINCIPAL DISPLAY PANEL - 15 mg Tablet Bottle Label

Palladia®
(toceranib phosphate)

15 mg per tablet

Antineoplastic for Oral Use in Dogs Only
Caution: Federal (USA) law restricts this drug to
use by or on the order of a licensed veterinarian.

15 mg toceranib per tablet
NET CONTENTS: 30 Tablets

Approved by FDA under NADA # 141-295

zoetis

Palladia 15mg

PRINCIPAL DISPLAY PANEL - 50 mg Tablet Bottle Label

Palladia®
(toceranib phosphate)

50 mg per tablet

Antineoplastic for Oral Use in Dogs Only
Caution: Federal (USA) law restricts this drug to
use by or on the order of a licensed veterinarian.

50 mg toceranib per tablet
NET CONTENTS: 30 Tablets

Approved by FDA under NADA # 141-295

zoetis

Palladia 50mg